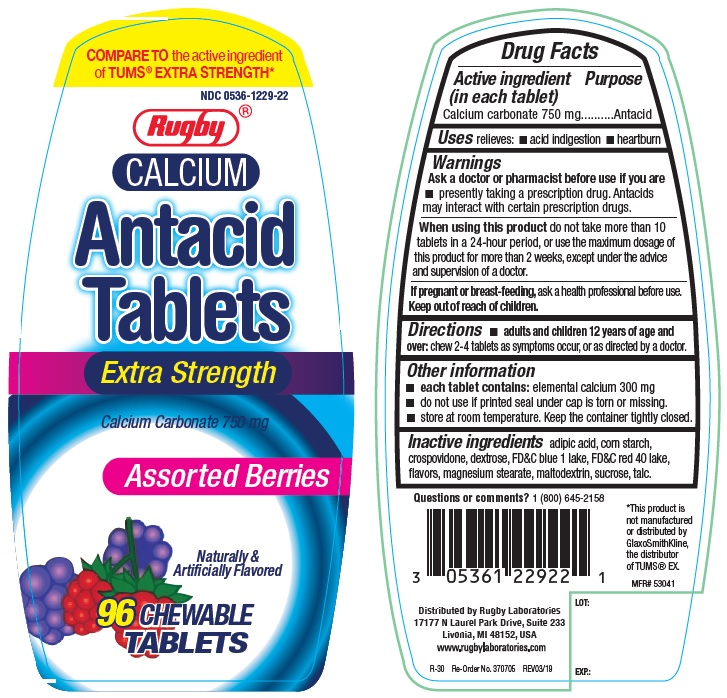 DRUG LABEL: Rugby Extra Strength Antacid
NDC: 0536-1229 | Form: TABLET, CHEWABLE
Manufacturer: Rugby Laboratories
Category: otc | Type: Human OTC Drug Label
Date: 20250821

ACTIVE INGREDIENTS: CALCIUM CARBONATE 750 mg/1 1
INACTIVE INGREDIENTS: ADIPIC ACID; STARCH, CORN; CROSPOVIDONE; DEXTROSE, UNSPECIFIED FORM; FD&C BLUE NO. 1; FD&C RED NO. 40; MAGNESIUM STEARATE; MALTODEXTRIN; SUCROSE; TALC

Rugby Extra Strength Antacid Assorted Berry Chewable Tablets

ACTIVE INGREDIENT (in each tablet)

Calcium carbonate 750 mg

PURPOSE

Antacid

USE(S)

relieves:

- acid indigestion
- heartburn

WARNINGS

.

ASK A DOCTOR OR PHARMACIST BEFORE USE IF YOU ARE

- presently taking a prescription drug. Antacids may interact with certain prescription drugs.

WHEN USING THIS PRODUCT

do not take more than 10 tablets in a 24-hour period, or use the maximum dosage of this product for more than 2 weeks, except under the advice and supervision of a doctor.

IF PREGNANT OR/BREASTFEEDING,

ask a health professional before use.

KEEP OUT OF REACH OF CHILDREN

.

DIRECTIONS

- adults and children 12 years of age and over: chew 2-4 tablets as symptoms occur, or as directed by a doctor.

OTHER INFORMATION

- each tablet contains: elemental calcium 300 mg
- do not use if printed seal under the cap is torn or missing
- store at room temperature. keep the container tightly closed.

INACTIVE INGREDIENTS

adipic acid, corn starch, crospovidone, dextrose, FD&C blue 1 lake, FD&C red 40 lake, flavors, magnesium stearate, maltodextrin, sucrose, talc.

PRINCIPAL DISPLAY PANEL

COMPARE TO the active ingredient of TUMS® EXTRA STRENGTH*
NDC 0536-1229-22
Rugby
CALCIUM
Antacid Tablets
Extra Strength
Calcium Carbonate 750 mg
Assorted Berries
Naturally & Artificially Flavored
96 CHEWABLE TABLETS